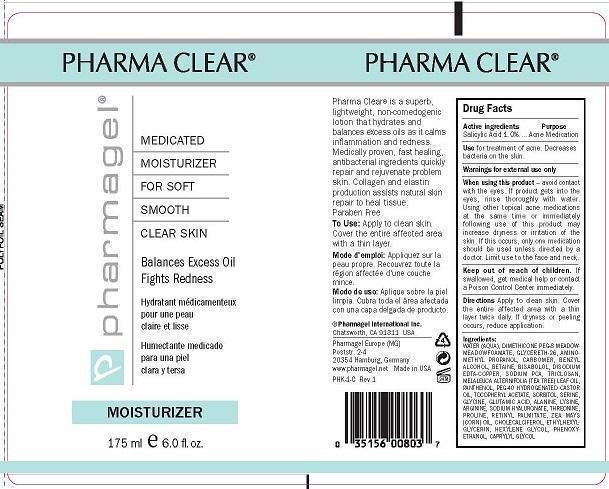 DRUG LABEL: PHARMA CLEAR MOISTURIZER
NDC: 67879-103 | Form: LOTION
Manufacturer: PHARMAGEL INTERNATIONAL INC
Category: otc | Type: HUMAN OTC DRUG LABEL
Date: 20240813

ACTIVE INGREDIENTS: SALICYLIC ACID 1 g/100 mL
INACTIVE INGREDIENTS: WATER; DIMETHICONE PEG-8 LAURATE; GLYCERETH-26; AMINOMETHYLPROPANOL; CARBOMER HOMOPOLYMER TYPE C (ALLYL PENTAERYTHRITOL CROSSLINKED); BENZYL ALCOHOL; BETAINE; LEVOMENOL; DISODIUM EDTA-COPPER; SODIUM PYRROLIDONE CARBOXYLATE; TRICLOSAN; TEA TREE OIL; PANTHENOL; POLYOXYL 40 HYDROGENATED CASTOR OIL; .ALPHA.-TOCOPHEROL ACETATE; SORBITOL; SERINE; GLYCINE; GLUTAMIC ACID; ALANINE; LYSINE; ARGININE; HYALURONATE SODIUM; THREONINE; PROLINE; VITAMIN A PALMITATE; CORN OIL; CHOLECALCIFEROL; ETHYLHEXYLGLYCERIN; HEXYLENE GLYCOL; PHENOXYETHANOL; CAPRYLYL GLYCOL

PHARMAGEL - PHARMA CLEAR MOISTURIZER (67879-103)

ACTIVE INGREDIENTS

Salicylic Acid 1.0%

PURPOSE

Acne Medication

Uses

Use for treatment of acne. Decreases bacteria on the skin.

WARNINGS

Warning: For external use only

When using this product:

• avoid contact with the eyes. If product gets into the eyes, rinse thoroughly with water.

• Using other topical acne medications at the same time or immediately following use of this product may increase dryness or irritation of the

skin. If this occurs, only one medication should be used unless directed by a doctor.

• Limit use to the face and neck.

Keep out of reach of children. If swallowed, get medical help or contact a Poison Control Center immediately.

Directions:

Apply to clean skin. Cover the entire affected area with a thin layer twice daily. If dryness or peeling occurs, reduce application.

INACTIVE INGREDIENTS:

WATER (AQUA), DIMETHICONE PEG-8 MEADOWMEADOWFOAMATE, GLYCERETH-26, AMINOMETHYL PROPANOL, CARBOMER, BENZYL ALCOHOL, BETAINE, BISABOLOL, DISODIUM EDTA-COPPER, SODIUM PCA, TRICLOSAN, MELALEUCA ALTERNIFOLIA (TEA TREE) LEAF OIL, PANTHENOL, PEG-40 HYDROGENATED CASTOR OIL, TOCOPHERYL ACETATE, SORBITOL, SERINE, GLYCINE, GLUTAMIC ACID, ALANINE, LYSINE, ARGININE, SODIUM HYALURONATE, THREONINE, PROLINE, RETINYL PALMITATE, ZEA MAYS (CORN) OIL, CHOLECALCIFEROL, ETHYLHEXYLGLYCERIN, HEXYLENE GLYCOL, PHENOXYETHANOL, CAPRYLYL GLYCOL